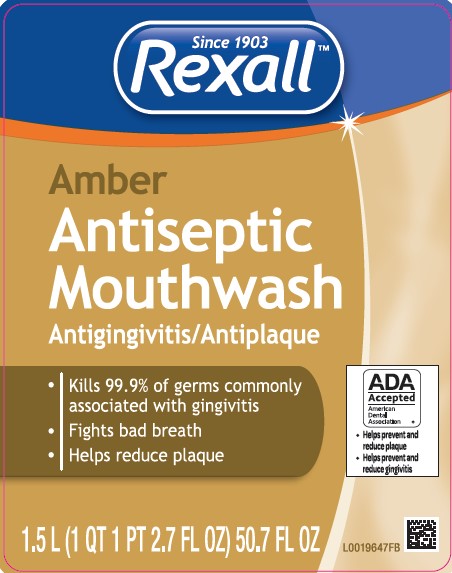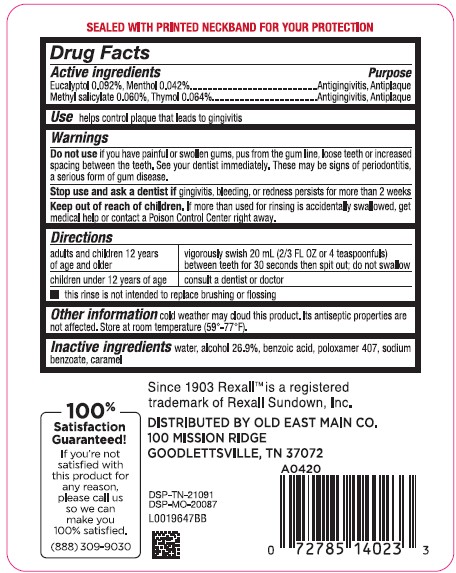 DRUG LABEL: Mouth Rinse
NDC: 55910-318 | Form: MOUTHWASH
Manufacturer: Old East Main Co.
Category: otc | Type: HUMAN OTC DRUG LABEL
Date: 20260302

ACTIVE INGREDIENTS: EUCALYPTOL 0.92 mg/1 mL; MENTHOL 0.42 mg/1 mL; METHYL SALICYLATE 0.6 mg/1 mL; THYMOL 0.64 mg/1 mL
INACTIVE INGREDIENTS: WATER; ALCOHOL; BENZOIC ACID; POLOXAMER 407; SODIUM BENZOATE; CARAMEL

Rexall 318.003/318AH-AI
Antiseptic Mouthrinse

Tamper Evident Statement

SEALED WITH PRINTED NECKBAND FOR YOUR PROTECTION

Active ingredient

Eucalyptol 0.092%

Menthol 0.042%

Methyl salicylate 0.060%

Thymol 0.064%

Purpose

Antigingivitis, Antiplaque

Use

helps control plaque that leads to gingivitis

Warnings

for this product

Do not use

if you have painful or swollen gums, pus from the gum line, loose teeth or increased spacing between the teeth. See your dentist immediately. These may be signs of periodontitis, a serious form of gum disease.

Stop use and ask a dentist if

gingivitis, bleeding, or redness persists for more than 2 weeks

Keep out of reach of children.

If more than used for rinsing is accidentally swallowed, get medical help or contact a Poison Control Center right away.

Directions

adults and children 12 years and older - vigorously swish 20 mL (2/3 FL OZ or 4 teaspoonfuls) between teeth for 30 seconds then spit out; do not swallow
children under 12 years of age - consult a dentist or doctor

• this rinse is not intended to replace brushing or flossing

Other information

cold weather may cloud this product. Its antiseptic properties are not affected. Store at room temperature (59⁰-77⁰F).

Inactive ingredients

water, alcohol 26.9%, benzoic acid, poloxamer 407, sodium benzoate, caramel

ADVERSE REACTION

100% Satisfaction Guaranteed

If you're not satisfied with this product for any reason, please call us so we can make you 100% satisfied.

(888)309-9030

Since 1903 Rexall is a registered trademark of Rexall Sundown, Inc.

Distributed by Old East Main Co.

100 Mission Ridge

Goodlettsville, TN 37072

DSP-TN-21091

DSP-MO-20087

Principal display panel

Since 1903

Rexall™

Amber

Antiseptic

Mouthwash

Antigingivitis/Antiplaque

- Kills 99.9% of germs commonly associated with gingivitis
- Fights bad breath
- Helps reduce plaque

ADA Accepted

Amrican Dental Association

- Helps prevent and reduce plaque
- Helps prevent and reduce gingivitis

1.5 L (1 QT 1 PT 2.7 FL OZ) 50.7 FL OZ